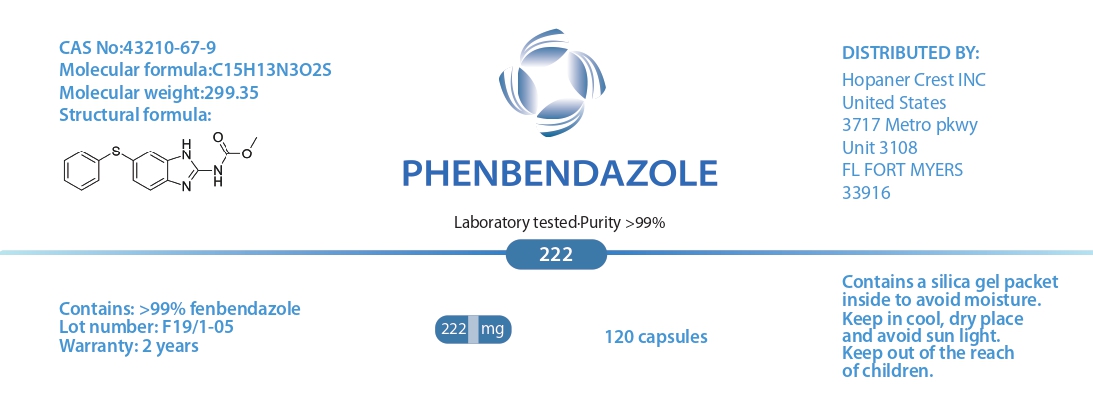 DRUG LABEL: PHENBENDAZOLE
NDC: 86202-3107 | Form: TABLET
Manufacturer: AMBIENCE FAMILY INC
Category: animal | Type: OTC ANIMAL DRUG LABEL
Date: 20240501

ACTIVE INGREDIENTS: fenbendazole 219 g/222 g

PHENBENDAZOLE

WARNINGS AND PRECAUTIONS

Contains a silica gel packet inside to avoid moisture.
Keep in cool, dry place and avoid sun light.
Keep out of the reach of children.

CAS No:43210-67-9
Molecular formula:C15H13N3O2S
Molecular weight:299.35

DISTRIBUTED BY:
Hopaner Crest INC
United States
3717 Metro pkwy
Unit 3108
FL FORT MYERS
33916

WARNINGS AND PRECAUTIONS

Not for use in humans. Keep out of reach of children. Protective gloves should be used and care should be taken when handling the product to avoid skin and eye exposure and accidental ingestion. Accidental exposure may result in skin and eye irritation. Accidental ingestion may cause gastrointestinal disturbances and hypersensitivity reactions in humans.

PACKAGE LABEL

Laboratory tested·Purity >99%

Contains: >99% fenbendazole
Lot number: F19/1-05
Warranty: 2 years